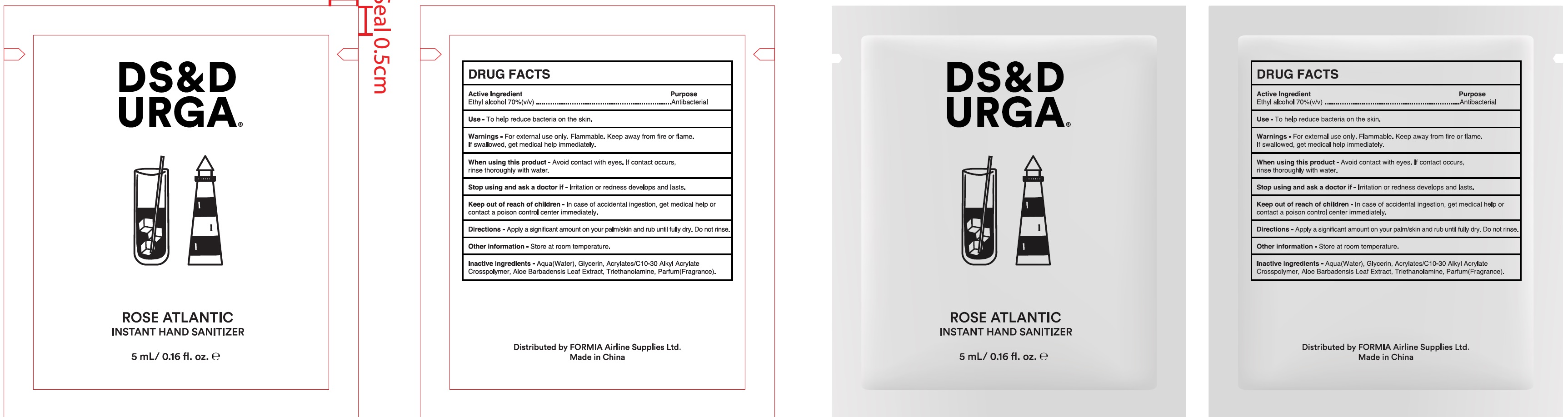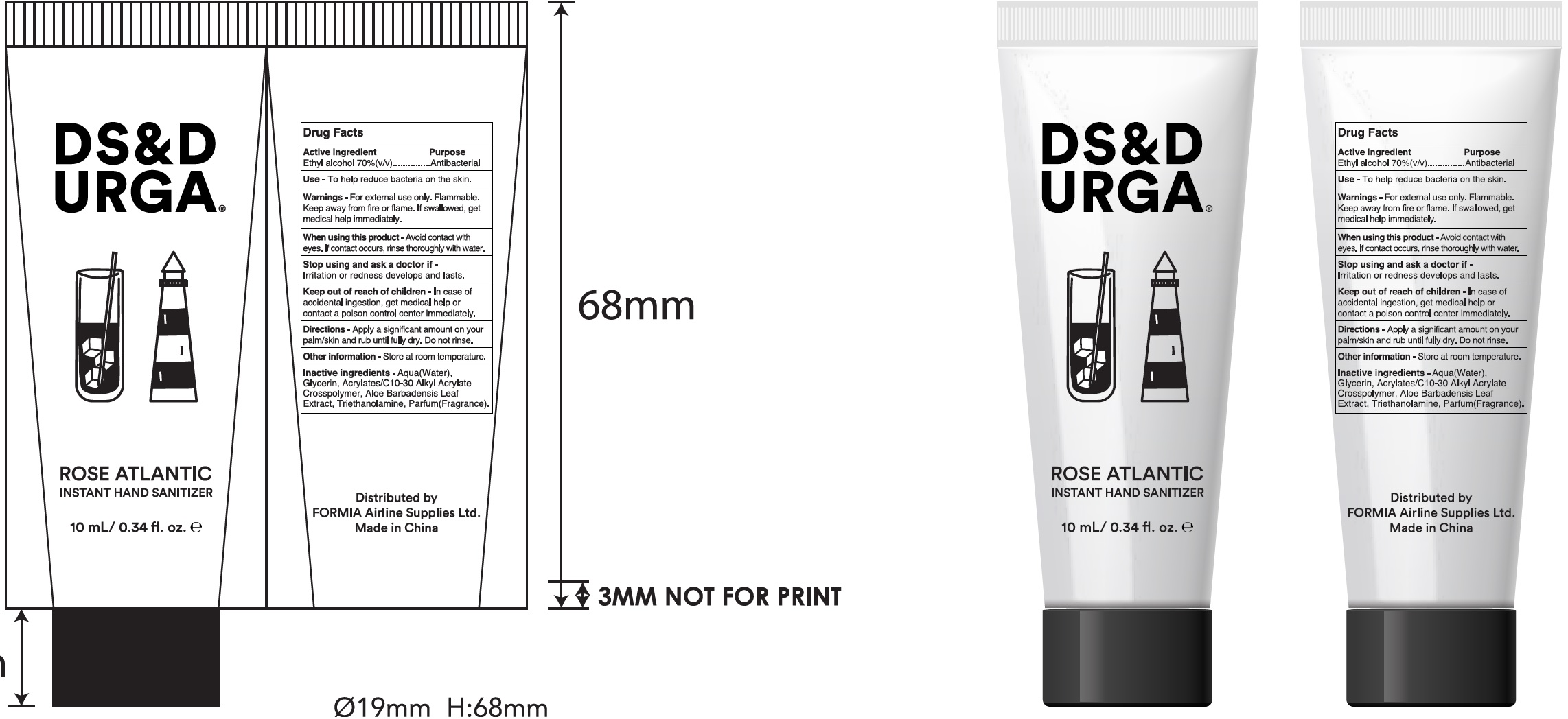 DRUG LABEL: Instant Hand Sanitizer
NDC: 79940-000 | Form: GEL
Manufacturer: FORMIA Airline Supplies Ltd
Category: otc | Type: HUMAN OTC DRUG LABEL
Date: 20200820

ACTIVE INGREDIENTS: ALCOHOL 0.7 mL/1 mL
INACTIVE INGREDIENTS: WATER; GLYCERIN; CARBOMER INTERPOLYMER TYPE A (ALLYL SUCROSE CROSSLINKED); ALOE VERA LEAF; TROLAMINE

Instant Hand Sanitizer

Active Ingredient

Ethyl alcohol 70% (v/v)

Purpose

Antibacterial

Use

-To help reduce bacteria on the skin.

Warnings

- For external use only. Flammable. Keep away from fire or flame. If swallowed, get medical help immediately.

When using this product

- Avoid contact with eyes. If contact occurs, rinse thoroughly with water.

Stop using and ask a doctor if

Irritation or redess develops and lasts.

Keep out of reach of children.

- In case of accidental ingestion, get medical help or contact a poison control center immediately.

Directions

- Apply a significant amount on your palm/skin and rub until dry. Do not rinse.

Other information

- Store at room temperature.

Inactive ingredients

- Aqua(Water), Glycerin, Acylates/C10-30 Alkyl Acrylate Crosspolymer, Aloe Barbadensis Leaf Extract, Triethanolamine, Parfum(Fragrance).